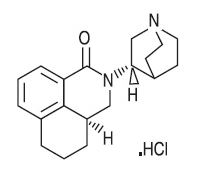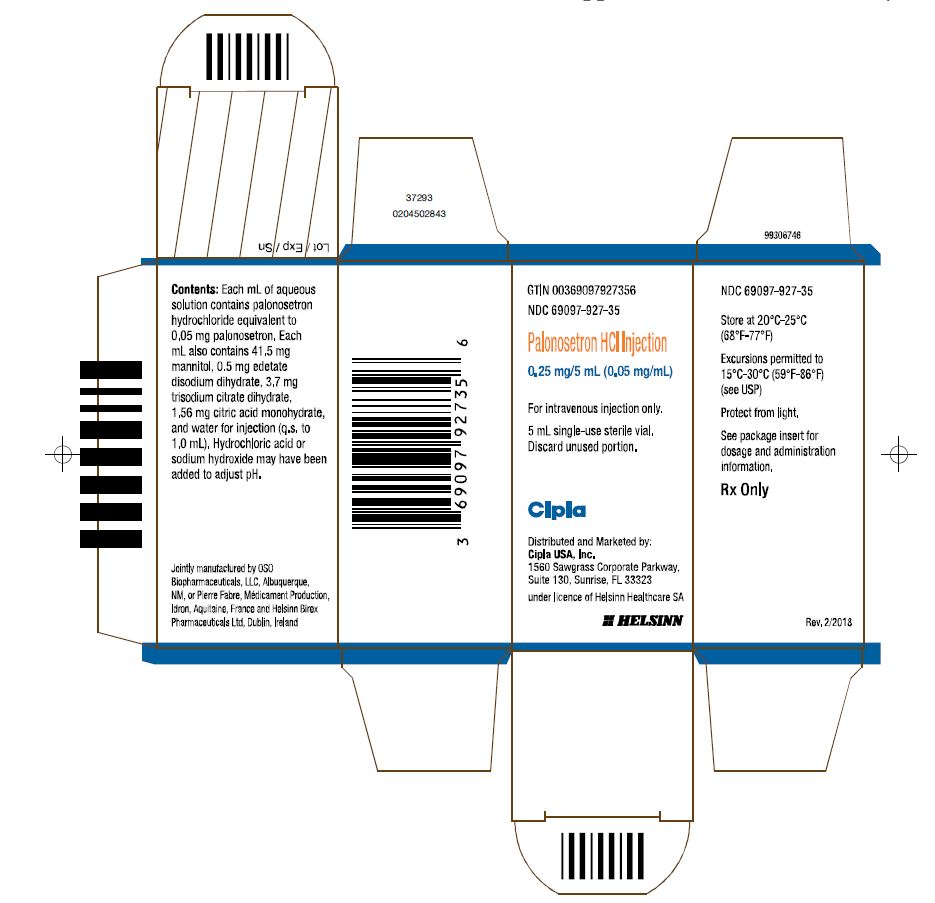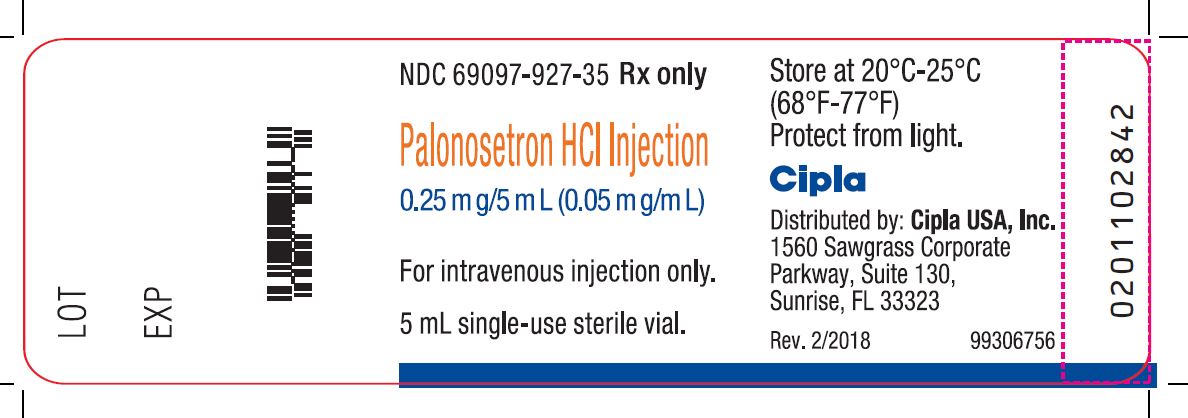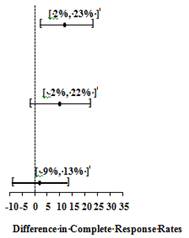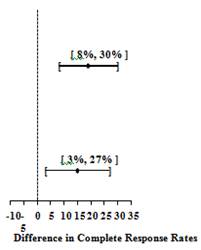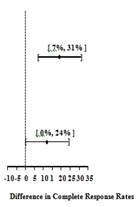 DRUG LABEL: palonosetron hydrochloride
NDC: 69097-927 | Form: INJECTION
Manufacturer: Cipla USA Inc.
Category: prescription | Type: HUMAN PRESCRIPTION DRUG LABEL
Date: 20220113

ACTIVE INGREDIENTS: PALONOSETRON HYDROCHLORIDE 0.25 mg/5 mL
INACTIVE INGREDIENTS: MANNITOL; EDETATE DISODIUM; CITRIC ACID MONOHYDRATE; SODIUM CITRATE; WATER

HIGHLIGHTS OF PRESCRIBING INFORMATION

These highlights do not include all the information needed to use PALONOSETRON HYDROCHLORIDE INJECTION safely and effectively. See full prescribing information for PALONOSETRON HYDROCHLORIDE INJECTION&#60;BR&#62;&#60;BR&#62;Palonosetron Hydrochloride Injection, for Intravenous Use&#60;BR&#62;Initial U.S. Approval: 2003

RECENT MAJOR CHANGES

Indication (1.2) 05/2014

Dosage and Administration, Pediatric Cancer Patients (2.1) 05/2014

Warnings and Precautions, Serotonin Syndrome (5.2) 09/2014

1 INDICATIONS AND USAGE

Palonosetron Hydrochloride Injection is a serotonin-3 (5-HT3) receptor antagonist indicated in adults for:

- Moderately emetogenic cancer chemotherapy - prevention of acute and delayed nausea and vomiting associated with initial and repeat courses (1.1)
- Highly emetogenic cancer chemotherapy - prevention of acute nausea and vomiting associated with initial and repeat courses (1.1)
- Prevention of postoperative nausea and vomiting (PONV) for up to 24 hours following surgery. Efficacy beyond 24 hours has not been demonstrated (1.3)

Palonosetron Hydrochloride Injection is indicated in pediatric patients aged 1 month to less than 17 years for:

- Prevention of acute nausea and vomiting associated with initial and repeat courses of emetogenic cancer chemotherapy, including highly emetogenic cancer chemotherapy (1.2)

2 DOSAGE AND ADMINISTRATION

Chemotherapy-Induced Nausea and Vomiting (2.1)

Age | Dose* | Infusion Time
Adults | 0 . 2 5 mg x 1 | Infuse over 30 seconds beginning approx. 30 min before the start of chemo
Pediatrics (1 month to less than 17 years) | 2 0 micrograms per k ilogram (max 1.5 mg) x 1 | Infuse over 15 minutes beginning approx. 30 min before the start of chemo
*Note different dosing units in pediatrics

Postoperative Nausea and Vomiting (2.1)

- Adult Dosage: a single 0.075 mg intravenous dose administered over 10 seconds immediately before the induction of anesthesia.

3 DOSAGE FORM AND STRENGTHS

0.25 mg/5mL (free base) single-use vial (3)

4 CONTRAINDICATIONS

Palonosetron Hydrochloride Injection is contraindicated in patients known to have hypersensitivity to the drug or any of its components (4)

5 WARNINGS AND PRECAUTIONS

- Hypersensitivity reactions, including anaphylaxis, have been reported with or without known hypersensitivity to other selective 5-HT3 receptor antagonists (5.1)
- Serotonin syndrome has been reported with 5-HT3receptor antagonists alone but particularly with concomitant use of serotonergic drugs (5.2)

6 ADVERSE REACTIONS

The most common adverse reactions in chemotherapy-induced nausea and vomiting in adults (incidence ≥5%) are headache and constipation (6.1).

The most common adverse reactions in postoperative nausea and vomiting (incidence ≥ 2%) are QT prolongation, bradycardia, headache, and constipation (6.2).

To report SUSPECTED ADVERSE REACTIONS, contact Cipla USA, Inc., at 1-866-604-3268 or FDA at 1-800-FDA-1088 or www.fda.gov/medwatch.

7 DRUG INTERACTIONS

The potential for clinically significant drug interactions with palonosetron appears to be low (7)

8 USE IN SPECIFIC POPULATIONS

Chemotherapy-Induced Nausea and Vomiting

Pediatric use: Safety and effectiveness in neonates (less than 1 month of age) have not been established (8.4)

Postoperative Nausea and Vomiting

Safety and Effectiveness in patients below the age of 18 years have not been established (8.4)

FULL PRESCRIBING INFORMATION

1 INDICATIONS AND USAGE

1.1 Chemotherapy-Induced Nausea and Vomiting in Adults

Palonosetron Hydrochloride Injection is indicated for:

- Moderately emetogenic cancer chemotherapy -- prevention of acute and delayed nausea and vomiting associated with initial and repeat courses
- Highly emetogenic cancer chemotherapy -- prevention of acute nausea and vomiting associated with initial and repeat courses

1.2 Chemotherapy-Induced Nausea and Vomiting in Pediatric Patients Aged 1 Month to Less than 17 Years

Palonosetron Hydrochloride Injection is indicated for prevention of acute nausea and vomiting associated with initial and repeat courses of emetogenic cancer chemotherapy, including highly emetogenic cancer chemotherapy.

1.3 Postoperative Nausea and Vomiting in Adults

Palonosetron Hydrochloride Injection is indicated for prevention of postoperative nausea and vomiting (PONV) for up to 24 hours following surgery. Efficacy beyond 24 hours has not been demonstrated.

As with other antiemetics, routine prophylaxis is not recommended in patients in whom there is little expectation that nausea and/or vomiting will occur postoperatively. In patients where nausea and vomiting must be avoided during the postoperative period, Palonosetron Hydrochloride Injection is recommended even where the incidence of postoperative nausea and/or vomiting is low.

2 DOSAGE AND ADMINISTRATION

2.1 Recommended Dosing

Chemotherapy-Induced Nausea and Vomiting

Age | Dose* | Infusion Time
Adults | 0 . 2 5 mg x 1 | Infuse over 30 seconds beginning approx. 30 min before the start of chemo
Pediatrics (1 month to less than 17 years) | 2 0 micrograms per kilogram (max 1.5 mg) x 1 | Infuse over 15 minutes beginning approx. 30 min before the start of chemo
*Note different dosing units in pediatrics

Postoperative Nausea and Vomiting

Dosage for Adults - a single 0.075 mg intravenous dose administered over 10 seconds immediately before the induction of anesthesia.

2.2 Instructions for Intravenous Administration

Palonosetron Hydrochloride Injection is supplied ready for intravenous administration at a concentration of 0.05 mg/mL (50 mcg/ mL). Palonosetron Hydrochloride Injection should not be mixed with other drugs. The infusion line should be flushed with normal saline before and after administration of Palonosetron Hydrochloride Injection. Parenteral drug products should be inspected visually for particulate matter and discoloration before administration, whenever solution and container permit.

3 DOSAGE FORM AND STRENGTHS

Palonosetron Hydrochloride Injection is supplied as a single-use sterile, clear, colorless solution in glass vials that provide:

- 0.25 mg (free base) per 5 mL (concentration: 0.05 mg/mL, 50 mcg/mL)

4 CONTRAINDICATIONS

Palonosetron Hydrochloride Injection is contraindicated in patients known to have hypersensitivity to the drug or any of its components. [see Adverse Reactions (6.2)].

5 WARNINGS AND PRECAUTIONS

5.1 Hypersensitivity

Hypersensitivity reactions, including anaphylaxis, have been reported with or without known hypersensitivity to other 5-HT3 receptor antagonists.

5.2 Serotonin Syndrome

The development of serotonin syndrome has been reported with 5-HT3 receptor antagonists. Most reports have been associated with concomitant use of serotonergic drugs (e.g., selective serotonin reuptake inhibitors (SSRIs), serotonin and norepinephrine reuptake inhibitors (SNRIs), monoamine oxidase inhibitors, mirtazapine, fentanyl, lithium, tramadol, and intravenous methylene blue). Some of the reported cases were fatal. Serotonin syndrome occurring with overdose of another 5-HT3 receptor antagonist alone has also been reported. The majority of reports of serotonin syndrome related to 5-HT3 receptor antagonist use occurred in a post-anesthesia care unit or an infusion center.

Symptoms associated with serotonin syndrome may include the following combination of signs and symptoms: mental status changes (e.g. agitation, hallucinations, delirium, and coma), autonomic instability (e.g., tachycardia, labile blood pressure, dizziness, diaphoresis, flushing, hyperthermia), neuromuscular symptoms (e.g., tremor, rigidity, myoclonus, hyperreflexia, incoordination), seizures, with or without gastrointestinal symptoms (e.g., nausea, vomiting, diarrhea). Patients should be monitored for the emergence of serotonin syndrome, especially with concomitant use of Palonosetron Hydrochloride Injection and other serotonergic drugs. If symptoms of serotonin syndrome occur, discontinue Palonosetron Hydrochloride Injection and initiate supportive treatment. Patients should be informed of the increased risk of serotonin syndrome, especially if Palonosetron Hydrochloride Injection is used concomitantly with other serotonergic drugs [see Drug Interactions (7), Patient Counseling Information (17)].

6 ADVERSE REACTIONS

Because clinical trials are conducted under widely varying conditions, adverse reaction rates observed in the clinical trials of a drug cannot be directly compared to rates in the clinical trials of another drug and may not reflect the rates observed in practice.

6.1 Chemotherapy-Induced Nausea and Vomiting

Adults

In clinical trials for the prevention of nausea and vomiting induced by moderately or highly emetogenic chemotherapy, 1374 adult patients received palonosetron. Adverse reactions were similar in frequency and severity with Palonosetron Hydrochloride Injection and ondansetron or dolasetron. Following is a listing of all adverse reactions reported by 2% of patients in these trials (Table 1).

Table 1: Adverse Reactions from Chemotherapy-Induced Nausea and Vomiting Studies ≥ 2% in any Treatment Group
Event | Palonosetron Hydrochloride Injection 0.25 mg (N=633) | Ondansetron 32 mg I.V. (N=410) | Dolasetron 100 mg I.V. (N=194)
Headache | 60 (9%) | 34 (8%) | 32 (16%)
Constipation | 29 (5%) | 8 (2%) | 12 (6%)
Diarrhea | 8 (1%) | 7 (2%) | 4 (2%)
Dizziness | 8 (1%) | 9 (2%) | 4 (2%)
Fatigue | 3 (< 1%) | 4 (1%) | 4 (2%)
Abdominal Pain | 1 (< 1%) | 2 (< 1%) | 3 (2%)
Insomnia | 1 (< 1%) | 3 (1%) | 3 (2%)

In other studies, 2 subjects experienced severe constipation following a single palonosetron dose of approximately 0.75 mg, three times the recommended dose. One patient received a 10 mcg/kg oral dose in a post-operative nausea and vomiting study and one healthy subject received a 0.75 mg I.V. dose in a pharmacokinetic study.

In clinical trials, the following infrequently reported adverse reactions, assessed by investigators as treatment-related or causality unknown, occurred following administration of Palonosetron Hydrochloride Injection to adult patients receiving concomitant cancer chemotherapy:

Cardiovascular: 1%: non-sustained tachycardia, bradycardia, hypotension, < 1%: hypertension, myocardial ischemia, extrasystoles, sinus tachycardia, sinus arrhythmia, supraventricular extrasystoles and QT prolongation. In many cases, the relationship to Palonosetron Hydrochloride Injection was unclear.

Dermatological: < 1%: allergic dermatitis, rash.

Hearing and Vision: < 1%: motion sickness, tinnitus, eye irritation and amblyopia.

Gastrointestinal System: 1%: diarrhea, < 1%: dyspepsia, abdominal pain, dry mouth, hiccups and flatulence.

General: 1%: weakness, < 1%: fatigue, fever, hot flash, flu-like syndrome.

Liver: < 1%: transient, asymptomatic increases in AST and/or ALT and bilirubin. These changes occurred predominantly in patients receiving highly emetogenic chemotherapy.

Metabolic: 1%: hyperkalemia, < 1%: electrolyte fluctuations, hyperglycemia, metabolic acidosis, glycosuria, appetite decrease, anorexia.

Musculoskeletal: < 1%: arthralgia.

Nervous System: 1%: dizziness, < 1%: somnolence, insomnia, hypersomnia, paresthesia.

Psychiatric: 1%: anxiety, < 1%: euphoric mood.

Urinary System: < 1%: urinary retention.

Vascular: < 1%: vein discoloration, vein distention.

Pediatrics

In a pediatric clinical trial for the prevention of chemotherapy-induced nausea and vomiting 163 cancer patients received a single 20 mcg/kg (maximum 1.5 mg) intravenous infusion of palonosetron 30 minutes before beginning the first cycle of emetogenic chemotherapy. Patients had a mean age of 8.4 years (range 2 months to 16.9 years) and were 46% male; and 93% white.

The following adverse reactions were reported for palonosetron:

Nervous System: <1%: headache, dizziness, dyskinesia.

General: <1%: infusion site pain.

Dermatological: <1%: allergic dermatitis, skin disorder.

In the trial, adverse reactions were evaluated in pediatric patients receiving palonosetron for up to 4 chemotherapy cycles.

6.2 Postoperative Nausea and Vomiting

The adverse reactions cited in Table 2 were reported in ≥ 2% of adults receiving I.V. Palonosetron Hydrochloride Injection 0.075 mg immediately before induction of anesthesia in one phase 2 and two phase 3 randomized placebo-controlled trials. Rates of events between palonosetron and placebo groups were similar. Some events are known to be associated with, or may be exacerbated by concomitant perioperative and intraoperative medications administered in this surgical population. Please refer to Section 12.2, thorough QT/QTc study results, for data demonstrating the lack of palonosetron effect on QT/QTc.

Table 2: Adverse Reactions from Postoperative Nausea and Vomiting Studies ≥ 2% in any Treatment Group
Event | Palonosetron Hydrochloride Injection 0.075 mg (N=336) | Placebo (N=369)
Electrocardiogram QT prolongation | 16 (5%) | 11 (3%)
Bradycardia | 13 (4%) | 16 (4%)
Headache | 11 (3%) | 14 (4%)
Constipation | 8 (2%) | 11(3%)

In these clinical trials, the following infrequently reported adverse reactions, assessed by investigators as treatment-related or causality unknown, occurred following administration of Palonosetron Hydrochloride Injection to adult patients receiving concomitant perioperative and intraoperative medications including those associated with anesthesia:

Cardiovascular: 1%: electrocardiogram QTc prolongation, sinus bradycardia, tachycardia, < 1%: blood pressure decreased, hypotension, hypertension, arrhythmia, ventricular extrasystoles, generalized edema, ECG T wave amplitude decreased, platelet count decreased. The frequency of these adverse effects did not appear to be different from placebo.

Dermatological: 1%: pruritus.

Gastrointestinal System: 1%: flatulence, < 1%: dry mouth, upper abdominal pain, salivary hypersecretion, dyspepsia, diarrhea, intestinal hypomotility, anorexia.

General: < 1%: chills.

Liver: 1%: increases in AST and/or ALT, < 1%: hepatic enzyme increased.

Metabolic: < 1%: hypokalemia, anorexia.

Nervous System: < 1%: dizziness.

Respiratory: < 1%: hypoventilation, laryngospasm.

Urinary System: 1%: urinary retention.

6.3 Postmarketing Experience

The following adverse reactions have been identified during postapproval use of Palonosetron Hydrochloride Injection. Because these reactions are reported voluntarily from a population of uncertain size, it is not always possible to reliably estimate their frequency or establish a causal relationship to drug exposure.

Very rare cases (<1/10,000) of hypersensitivity reactions including anaphylaxis and anaphylactic shock and injection site reactions (burning, induration, discomfort and pain) were reported from postmarketing experience of Palonosetron Hydrochloride Injection 0.25 mg in the prevention of chemotherapy-induced nausea and vomiting.

7 DRUG INTERACTIONS

Palonosetron is eliminated from the body through both renal excretion and metabolic pathways with the latter mediated via multiple CYP enzymes. Further in vitro studies indicated that palonosetron is not an inhibitor of CYP1A2, CYP2A6, CYP2B6, CYP2C9, CYP2D6, CYP2E1 and CYP3A4/5 (CYP2C19 was not investigated) nor does it induce the activity of CYP1A2, CYP2D6, or CYP3A4/5. Therefore, the potential for clinically significant drug interactions with palonosetron appears to be low.

Serotonin syndrome (including altered mental status, autonomic instability, and neuromuscular symptoms) has been described following the concomitant use of 5-HT3 receptor antagonists and other serotonergic drugs, including selective serotonin reuptake inhibitors (SSRIs) and serotonin and noradrenaline reuptake inhibitors (SNRIs) [see Warnings and Precautions (5.2)].

Coadministration of 0.25 mg I.V. palonosetron and 20 mg I.V. dexamethasone in healthy subjects revealed no pharmacokinetic drug-interactions between palonosetron and dexamethasone.

In an interaction study in healthy subjects where palonosetron 0.25 mg (I.V. bolus) was administered on day 1 and oral aprepitant for 3 days (125 mg/80 mg/80 mg), the pharmacokinetics of palonosetron were not significantly altered (AUC: no change, Cmax: 15% increase).

A study in healthy volunteers involving single-dose I.V. palonosetron (0.75 mg) and steady state oral metoclopramide (10 mg four times daily) demonstrated no significant pharmacokinetic interaction.

In controlled clinical trials, Palonosetron Hydrochloride Injection has been safely administered with corticosteroids, analgesics, antiemetics /antinauseants, antispasmodics and anticholinergic agents.

Palonosetron did not inhibit the antitumor activity of the five chemotherapeutic agents tested (cisplatin, cyclophosphamide, cytarabine, doxorubicin and mitomycin C) in murine tumor models.

8 USE IN SPECIFIC POPULATIONS

8.1 Pregnancy

Pregnancy Category B

Risk Summary

Adequate and well controlled studies with Palonosetron Hydrochloride Injection have not been conducted in pregnant women. In animal reproduction studies, no effects on embryo-fetal development were observed with the administration of oral palonosetron during the period of organogenesis at doses up to 1894 and 3789 times the recommended human intravenous dose in rats and rabbits, respectively. Because animal reproduction studies are not always predictive of human response, Palonosetron Hydrochloride Injection should be used during pregnancy only if clearly needed.

Animal Data

In animal studies, no effects on embryo-fetal development were observed in pregnant rats given oral palonosetron at doses up to 60 mg/kg/day (1894 times the recommended human intravenous dose based on body surface area) or pregnant rabbits given oral doses up to 60 mg/kg/day (3789 times the recommended human intravenous dose based on body surface area) during the period of organogenesis.

8.3 Nursing Mothers

It is not known whether Palonosetron Hydrochloride Injection is present in human milk. Because many drugs are excreted in human milk and because of the potential for serious adverse reactions in nursing infants and the potential for tumorigenicity shown for palonosetron in the rat carcinogenicity study [see Nonclinical Toxicology (13.1)], a decision should be made whether to discontinue nursing or to discontinue the drug, taking into account the importance of the drug to the mother.

8.4 Pediatric Use

Chemotherapy-Induced Nausea and Vomiting

Safety and effectiveness of Palonosetron Hydrochloride Injection have been established in pediatric patients aged 1 month to less than 17 years for the prevention of acute nausea and vomiting associated with initial and repeat courses of emetogenic cancer chemotherapy, including highly emetogenic cancer chemotherapy. Use is supported by a clinical trial where 165 pediatric patients aged 2 months to <17 years were randomized to receive a single dose of palonosetron 20 mcg/kg (maximum 1.5 mg) administered as an intravenous infusion 30 minutes prior to the start of emetogenic chemotherapy [see Clinical Studies (14.2)]. While this study demonstrated that pediatric patients require a higher palonosetron dose than adults to prevent chemotherapy-induced nausea and vomiting, the safety profile is consistent with the established profile in adults [see Adverse Reactions (6.1)].

Safety and effectiveness of Palonosetron Hydrochloride Injection in neonates (less than 1 month of age) have not been established.

Postoperative Nausea and Vomiting Studies

Safety and efficacy have not been established in pediatric patients for prevention of postoperative nausea and vomiting. Two pediatric trials were performed.

Pediatric Study 1, a dose finding study was conducted to compare two doses of palonosetron, 1 mcg/kg (max 0.075 mg) versus 3 mcg/kg (max 0.25 mg). A total of 150 pediatric surgical patients participated, age range 1 month to <17 years. No dose response was observed.

Pediatric Study 2, a multicenter, double-blind, double-dummy, randomized, parallel group, active control, single-dose non-inferiority study, compared I.V. palonosetron (1 mcg/kg, max 0.075 mg) versus I.V. ondansetron. A total of 670 pediatric surgical patients participated, age 30 days to <17 years. The primary efficacy endpoint, Complete Response (CR: no vomiting, no retching, and no antiemetic rescue medication) during the first 24 hours postoperatively was achieved in 78.2% of patients in the palonosetron group and 82.7% in the ondansetron group. Given the pre-specified non-inferiority margin of -10%, the stratum adjusted Mantel-Haenszel statistical non-inferiority confidence interval for the difference in the primary endpoint, complete response (CR), was [-10.5, 1.7%], therefore non-inferiority was not demonstrated. Adverse reactions to palonosetron were similar to those reported in adults (Table 2).

8.5 Geriatric Use

Population pharmacokinetics analysis did not reveal any differences in palonosetron pharmacokinetics between cancer patients ≥ 65 years of age and younger patients (18 to 64 years). Of the 1374 adult cancer patients in clinical studies of palonosetron, 316 (23%) were ≥ 65 years old, while 71 (5%) were ≥ 75 years old. No overall differences in safety or effectiveness were observed between these subjects and the younger subjects, but greater sensitivity in some older individuals cannot be ruled out. No dose adjustment or special monitoring are required for geriatric patients.

Of the 1520 adult patients in Palonosetron Hydrochloride Injection PONV clinical studies, 73 (5%) were ≥ 65 years old. No overall differences in safety were observed between older and younger subjects in these studies, though the possibility of heightened sensitivity in some older individuals cannot be excluded. No differences in efficacy were observed in geriatric patients for the CINV indication and none are expected for geriatric PONV patients. However, Palonosetron Hydrochloride Injection efficacy in geriatric patients has not been adequately evaluated.

8.6 Renal Impairment

Mild to moderate renal impairment does not significantly affect palonosetron pharmacokinetic parameters. Total systemic exposure increased by approximately 28% in severe renal impairment relative to healthy subjects. Dosage adjustment is not necessary in patients with any degree of renal impairment.

8.7 Hepatic Impairment

Hepatic impairment does not significantly affect total body clearance of palonosetron compared to the healthy subjects. Dosage adjustment is not necessary in patients with any degree of hepatic impairment.

8.8 Race

Intravenous palonosetron pharmacokinetics was characterized in twenty-four healthy Japanese subjects over the dose range of 3 – 90 mcg/kg. Total body clearance was 25% higher in Japanese subjects compared to Whites, however, no dose adjustment is required. The pharmacokinetics of palonosetron in Blacks has not been adequately characterized.

10 OVERDOSAGE

There is no known antidote to Palonosetron Hydrochloride Injection. Overdose should be managed with supportive care.

Fifty adult cancer patients were administered palonosetron at a dose of 90 mcg/kg (equivalent to 6 mg fixed dose) as part of a dose ranging study. This is approximately 25 times the recommended dose of 0.25 mg. This dose group had a similar incidence of adverse events compared to the other dose groups and no dose response effects were observed.

Dialysis studies have not been performed, however, due to the large volume of distribution, dialysis is unlikely to be an effective treatment for palonosetron overdose. A single intravenous dose of palonosetron at 30 mg/kg (947 and 474 times the human dose for rats and mice, respectively, based on body surface area) was lethal to rats and mice. The major signs of toxicity were convulsions, gasping, pallor, cyanosis and collapse.

11 DESCRIPTION

Palonosetron Hydrochloride Injection is an antiemetic and antinauseant agent. It is a serotonin-3 (5-HT3) receptor antagonist with a strong binding affinity for this receptor. Chemically, palonosetron hydrochloride is: (3aS)-2-[(S)-1-Azabicyclo [2.2.2]oct-3-yl]-2,3,3a,4,5,6-hexahydro-1-oxo-1Hbenz[de]isoquinoline hydrochloride. The empirical formula is C19H24N2O.HCl, with a molecular weight of 332.87. Palonosetron hydrochloride exists as a single isomer and has the following structural formula:

image

Palonosetron hydrochloride is a white to off-white crystalline powder. It is freely soluble in water, soluble in propylene glycol, and slightly soluble in ethanol and 2-propanol.

Palonosetron Hydrochloride Injection is a sterile, clear, colorless, non pyrogenic, isotonic, buffered solution for intravenous administration. Palonosetron Hydrochloride Injection is available as 5 mL single use vial. Each 5 mL vial contains 0.25 mg palonosetron base as 0.28 mg palonosetron hydrochloride, 207.5 mg mannitol, disodium edetate and citrate buffer in water for intravenous administration.

The pH of the solution in the 5 mL vials is 4.5 to 5.5.

12 CLINICAL PHARMACOLOGY

12.1 Mechanism of Action

Palonosetron is a 5-HT3 receptor antagonist with a strong binding affinity for this receptor and little or no affinity for other receptors.

Cancer chemotherapy may be associated with a high incidence of nausea and vomiting, particularly when certain agents, such as cisplatin, are used. 5-HT3 receptors are located on the nerve terminals of the vagus in the periphery and centrally in the chemoreceptor trigger zone of the area postrema. It is thought that chemotherapeutic agents produce nausea and vomiting by releasing serotonin from the enterochromaffin cells of the small intestine and that the released serotonin then activates 5-HT3 receptors located on vagal afferents to initiate the vomiting reflex.

Postoperative nausea and vomiting is influenced by multiple patient, surgical and anesthesia related factors and is triggered by release of 5-HT in a cascade of neuronal events involving both the central nervous system and the gastrointestinal tract. The 5-HT3 receptor has been demonstrated to selectively participate in the emetic response.

12.2 Pharmacodynamics

The effect of palonosetron on blood pressure, heart rate, and ECG parameters including QTc were comparable to ondansetron and dolasetron in CINV clinical trials. In PONV clinical trials the effect of palonosetron on the QTc interval was no different from placebo. In non-clinical studies palonosetron possesses the ability to block ion channels involved in ventricular de- and re‑polarization and to prolong action potential duration.

The effect of palonosetron on QTc interval was evaluated in a double blind, randomized, parallel, placebo and positive (moxifloxacin) controlled trial in adult men and women. The objective was to evaluate the ECG effects of I.V. administered palonosetron at single doses of 0.25, 0.75 or 2.25 mg in 221 healthy subjects. The study demonstrated no significant effect on any ECG interval including QTc duration (cardiac repolarization) at doses up to 2.25 mg.

12.3 Pharmacokinetics

After intravenous dosing of palonosetron in healthy subjects and cancer patients, an initial decline in plasma concentrations is followed by a slow elimination from the body. Mean maximum plasma concentration (Cmax) and area under the concentration-time curve (AUC0-∞) are generally dose-proportional over the dose range of 0.3–90 mcg/kg in healthy subjects and in cancer patients. Following single I.V. dose of palonosetron at 3 mcg/kg (or 0.21 mg/70 kg) to six cancer patients, mean (± SD) maximum plasma concentration was estimated to be 5630 ± 5480 ng/L and mean AUC was 35.8 ± 20.9 h mcg/L.

Following I.V. administration of palonosetron 0.25 mg once every other day for 3 doses in 11 cancer patients, the mean increase in plasma palonosetron concentration from Day 1 to Day 5 was 42±34%. Following I.V. administration of palonosetron 0.25 mg once daily for 3 days in 12 healthy subjects, the mean (±SD) increase in plasma palonosetron concentration from Day 1 to Day 3 was 110±45%.

After intravenous dosing of palonosetron in patients undergoing surgery (abdominal surgery or vaginal hysterectomy), the pharmacokinetic characteristics of palonosetron were similar to those observed in cancer patients.

Distribution

Palonosetron has a volume of distribution of approximately 8.3 ± 2.5 L/kg. Approximately 62% of palonosetron is bound to plasma proteins.

Metabolism

Palonosetron is eliminated by multiple routes with approximately 50% metabolized to form two primary metabolites: N-oxide-palonosetron and 6-S-hydroxy-palonosetron. These metabolites each have less than 1% of the 5-HT3 receptor antagonist activity of palonosetron. In vitro metabolism studies have suggested that CYP2D6 and to a lesser extent, CYP3A4 and CYP1A2 are involved in the metabolism of palonosetron. However, clinical pharmacokinetic parameters are not significantly different between poor and extensive metabolizers of CYP2D6 substrates.

Elimination

After a single intravenous dose of 10 mcg/kg [^14C]-palonosetron, approximately 80% of the dose was recovered within 144 hours in the urine with palonosetron representing approximately 40% of the administered dose. In healthy subjects, the total body clearance of palonosetron was 0.160 0.035 L/h/kg and renal clearance was 0.067 0.018 L/h/kg. Mean terminal elimination half‑life is approximately 40 hours.

Specific Populations

Pediatric Patients

Single-dose I.V. Palonosetron Hydrochloride Injection pharmacokinetic data was obtained from a subset of pediatric cancer patients that received 10 mcg/kg or 20 mcg/kg. When the dose was increased from 10 mcg/kg to 20 mcg/kg a dose-proportional increase in mean AUC was observed. Following single dose intravenous infusion of Palonosetron Hydrochloride Injection 20 mcg/kg, peak plasma concentrations (CT) reported at the end of the 15 minute infusion were highly variable in all age groups and tended to be lower in patients < 6 years than in older patients. Median half-life was 29.5 hours in overall age groups and ranged from about 20 to 30 hours across age groups after administration of 20 mcg/kg.

The total body clearance (L/h/kg) in patients 12 to 17 years old was similar to that in healthy adults. There are no apparent differences in volume of distribution when expressed as L/kg.

Table 3: Pharmacokinetics Parameters in Pediatric Cancer PatientsFollowing Intravenous Infusion of Palonosetron HydrochlorideInjection at 20 mcg/kg over 15 min
PK Parameter a | Pediatric Age Group
PK Parameter a | <2 y | 2 to <6 y | 6 to <12 y | 12 to <17 y
 | N=12 | N=42 | N=38 | N=44
CT b, ng/L | 9025 (197) | 9414 (252) | 16275 (203) | 11831 (176)
 |  | N=5 | N=7 | N=10
AUC0-∞, h·mcg/L |  | 103.5 (40.4) | 98.7 (47.7) | 124.5 (19.1)
 | N=6 | N=14 | N=13 | N=19
Clearance c, L/h/kg | 0.31 (34.7) | 0.23 (51.3) | 0.19 (46.8) | 0.16 (27.8)
Vss c, L/kg | 6.08 (36.5) | 5.29 (57.8) | 6.26 (40.0) | 6.20 (29.0)
a Geometric Mean (CV) except for t1/2 which is median values .
b CT is the plasma palonosetron concentration at the end of the 15 minute infusion.
c Clearance and Vss calculated from 10 and 20 mcg/kg and are weight adjusted.

13 NONCLINICAL TOXICOLOGY

13.1 Carcinogenesis, Mutagenesis, Impairment of Fertility

In a 104-week carcinogenicity study in CD-1 mice, animals were treated with oral doses of palonosetron at 10, 30 and 60 mg/kg/day. Treatment with palonosetron was not tumorigenic. The highest tested dose produced a systemic exposure to palonosetron (Plasma AUC) of about 150 to 289 times the human exposure (AUC= 29.8 h mcg/L) at the recommended intravenous dose of 0.25 mg. In a 104-week carcinogenicity study in Sprague-Dawley rats, male and female rats were treated with oral doses of 15, 30 and 60 mg/kg/day and 15, 45 and 90 mg/kg/day, respectively. The highest doses produced a systemic exposure to palonosetron (Plasma AUC) of 137 and 308 times the human exposure at the recommended dose. Treatment with palonosetron produced increased incidences of adrenal benign pheochromocytoma and combined benign and malignant pheochromocytoma, increased incidences of pancreatic Islet cell adenoma and combined adenoma and carcinoma and pituitary adenoma in male rats. In female rats, it produced hepatocellular adenoma and carcinoma and increased the incidences of thyroid C-cell adenoma and combined adenoma and carcinoma.

Palonosetron was not genotoxic in the Ames test, the Chinese hamster ovarian cell (CHO/HGPRT) forward mutation test, the ex vivo hepatocyte unscheduled DNA synthesis (UDS) test, or the mouse micronucleus test. It was, however, positive for clastogenic effects in the Chinese hamster ovarian (CHO) cell chromosomal aberration test.

Palonosetron at oral doses up to 60 mg/kg/day (about 1894 times the recommended human intravenous dose based on body surface area) was found to have no effect on fertility and reproductive performance of male and female rats.

14 CLINICAL STUDIES

14.1 Chemotherapy-Induced Nausea and Vomiting in Adults

Efficacy of single-dose palonosetron injection in preventing acute and delayed nausea and vomiting induced by both moderately and highly emetogenic chemotherapy was studied in three Phase 3 trials and one Phase 2 trial. In these double-blind studies, complete response rates (no emetic episodes and no rescue medication) and other efficacy parameters were assessed through at least 120 hours after administration of chemotherapy. The safety and efficacy of palonosetron in repeated courses of chemotherapy was also assessed.

Moderately Emetogenic Chemotherapy

Two Phase 3, double-blind trials involving 1132 patients compared single-dose I.V. Palonosetron Hydrochloride Injection with either single-dose I.V. ondansetron (study 1) or dolasetron (study 2) given 30 minutes prior to moderately emetogenic chemotherapy including carboplatin, cisplatin ≤ 50 mg/m^2, cyclophosphamide < 1500 mg/m^2, doxorubicin > 25 mg/m^2, epirubicin, irinotecan, and methotrexate > 250 mg/m^2. Concomitant corticosteroids were not administered prophylactically in study 1 and were only used by 4-6% of patients in study 2. The majority of patients in these studies were women (77%), White (65%) and naïve to previous chemotherapy (54%). The mean age was 55 years.

Highly Emetogenic Chemotherapy

A Phase 2, double-blind, dose-ranging study evaluated the efficacy of single-dose I.V. palonosetron from 0.3 to 90 mcg/kg (equivalent to < 0.1 mg to 6 mg fixed dose) in 161 chemotherapy-naïve adult cancer patients receiving highly-emetogenic chemotherapy (either cisplatin ≥ 70 mg/m^2 or cyclophosphamide > 1100 mg/m^2). Concomitant corticosteroids were not administered prophylactically. Analysis of data from this trial indicates that 0.25 mg is the lowest effective dose in preventing acute nausea and vomiting induced by highly emetogenic chemotherapy.

A Phase 3, double-blind trial involving 667 patients compared single-dose I.V. Palonosetron Hydrochloride Injection with single-dose I.V. ondansetron (study 3) given 30 minutes prior to highly emetogenic chemotherapy including cisplatin ≥ 60 mg/m^2, cyclophosphamide > 1500 mg/m^2, and dacarbazine. Corticosteroids were co-administered prophylactically before chemotherapy in 67% of patients. Of the 667 patients, 51% were women, 60% White, and 59% naïve to previous chemotherapy. The mean age was 52 years.

Efficacy Results

The antiemetic activity of Palonosetron Hydrochloride Injection was evaluated during the acute phase (0-24 hours) [Table 4], delayed phase (24-120 hours) [Table 5], and overall phase (0-120 hours) [Table 6] post-chemotherapy in Phase 3 trials.

Table 4: Prevention of Acute Nausea and Vomiting (0-24 hours): Complete Response Rates
Chemotherapy | Study | Treatment Group | N a | % with Complete Response | p-value b | 97.5% Confidence Interval Palonosetron Hydrochloride Injection minus Comparator c
Moderately Emetogenic | 1 | Palonosetron Hydrochloride Injection 0.25 mg | 189 | 81 | 0.009 | 97.5% Confidence Interval Palonosetron Hydrochloride Injection minus Comparator c
Moderately Emetogenic | 1 | Ondansetron 32 mg I.V. | 185 | 69 | 0.009 | 97.5% Confidence Interval Palonosetron Hydrochloride Injection minus Comparator c
Moderately Emetogenic | 2 | Palonosetron Hydrochloride Injection 0.25 mg | 189 | 63 | NS | 97.5% Confidence Interval Palonosetron Hydrochloride Injection minus Comparator c
Moderately Emetogenic | 2 | Dolasetron 100 mg I.V. | 191 | 53 | NS | 97.5% Confidence Interval Palonosetron Hydrochloride Injection minus Comparator c
Highly Emetogenic | 3 | Palonosetron Hydrochloride Injection 0.25 mg | 223 | 59 | NS | 97.5% Confidence Interval Palonosetron Hydrochloride Injection minus Comparator c
Highly Emetogenic | 3 | Ondansetron 32 mg I.V. | 221 | 57 | NS | 97.5% Confidence Interval Palonosetron Hydrochloride Injection minus Comparator c
a Intent-to-treat cohort
b 2-sided Fisher's exact test. Significance level at α=0.025.
c These studies were designed to show non-inferiority. A lower bound greater than –15% demonstrates non-inferiority between Palonosetron Hydrochloride Injection and comparator.

These studies show that Palonosetron Hydrochloride Injection was effective in the prevention of acute nausea and vomiting associated with initial and repeat courses of moderately and highly emetogenic cancer chemotherapy. In study 3, efficacy was greater when prophylactic corticosteroids were administered concomitantly. Clinical superiority over other 5-HT3 receptor antagonists has not been adequately demonstrated in the acute phase.

Table 5: Prevention of Delayed Nausea and Vomiting (24-120 hours): Complete Response Rates
Chemotherapy | Study | Treatment Group | N a | % with Complete Response | p-value b | 97.5% Confidence Interval Palonosetron Hydrochloride Injection minus Comparator c
Moderately Emetogenic | 1 | Palonosetron Hydrochloride Injection 0.25 mg | 189 | 74 | <0.001 | 97.5% Confidence Interval Palonosetron Hydrochloride Injection minus Comparator c
Moderately Emetogenic | 1 | Ondansetron 32 mg I.V. | 185 | 55 | <0.001 | 97.5% Confidence Interval Palonosetron Hydrochloride Injection minus Comparator c
Moderately Emetogenic | 2 | Palonosetron Hydrochloride Injection 0.25 mg | 189 | 54 | 0.004 | 97.5% Confidence Interval Palonosetron Hydrochloride Injection minus Comparator c
Moderately Emetogenic | 2 | Dolasetron 100 mg I.V. | 191 | 39 | 0.004 | 97.5% Confidence Interval Palonosetron Hydrochloride Injection minus Comparator c
a Intent-to-treat cohort
b 2-sided Fisher's exact test. Significance level at α=0.025.
c These studies were designed to show non-inferiority. A lower bound greater than –15% demonstrates non-inferiority between Palonosetron Hydrochloride Injection and comparator.

These studies show that Palonosetron Hydrochloride Injection was effective in the prevention of delayed nausea and vomiting associated with initial and repeat courses of moderately emetogenic chemotherapy.

Table 6: Prevention of Overall Nausea andVomiting (0-120 hours): Complete Response Rates
Chemotherapy | Study | Treatment Group | N a | % with Complete Response | p-value b | 97.5% Confidence Interval Palonosetron Hydrochloride Injection minus Comparator c
Moderately Emetogenic | 1 | Palonosetron Hydrochloride Injection 0.25 mg | 189 | 69 | <0.001 | 97.5% Confidence Interval Palonosetron Hydrochloride Injection minus Comparator c
Moderately Emetogenic | 1 | Ondansetron 32 mg I.V. | 185 | 50 | <0.001 | 97.5% Confidence Interval Palonosetron Hydrochloride Injection minus Comparator c
Moderately Emetogenic | 2 | Palonosetron Hydrochloride Injection 0.25 mg | 189 | 46 | 0.021 | 97.5% Confidence Interval Palonosetron Hydrochloride Injection minus Comparator c
Moderately Emetogenic | 2 | Dolasetron 100 mg I.V. | 191 | 34 | 0.021 | 97.5% Confidence Interval Palonosetron Hydrochloride Injection minus Comparator c
a Intent-to-treat cohort
b 2-sided Fisher's exact test. Significance level at α=0.025.
c These studies were designed to show non-inferiority. A lower bound greater than –15% demonstrates non-inferiority between Palonosetron Hydrochloride Injection and comparator.

These studies show that Palonosetron Hydrochloride Injection was effective in the prevention of nausea and vomiting throughout the 120 hours (5 days) following initial and repeat courses of moderately emetogenic cancer chemotherapy.

14.2 Chemotherapy-Induced Nausea and Vomiting in Pediatrics

One double-blind, active-controlled clinical trial was conducted in pediatric cancer patients. The total population (N = 327) had a mean age of 8.3 years (range 2 months to 16.9 years) and were 53% male; and 96% white. Patients were randomized and received a 20 mcg/kg (maximum 1.5 mg) intravenous infusion of Palonosetron Hydrochloride Injection 30 minutes prior to the start of emetogenic chemotherapy (followed by placebo infusions 4 and 8 hours after the dose of palonosetron) or 0.15 mg/kg of intravenous ondansetron 30 minutes prior to the start of emetogenic chemotherapy (followed by ondansetron 0.15 mg/kg infusions 4 and 8 hours after the first dose of ondansetron, with a maximum total dose of 32 mg). Emetogenic chemotherapies administered included doxorubicin, cyclophosphamide (<1500 mg/m^2), ifosfamide, cisplatin, dactinomycin, carboplatin, and daunorubicin. Adjuvant corticosteroids, including dexamethasone, were administered with chemotherapy in 55% of patients.

Complete Response in the acute phase of the first cycle of chemotherapy was defined as no vomiting, no retching, and no rescue medication in the first 24 hours after starting chemotherapy. Efficacy was based on demonstrating non-inferiority of intravenous palonosetron compared to intravenous ondansetron. Non-inferiority criteria were met if the lower bound of the 97.5% confidence interval for the difference in Complete Response rates of intravenous palonosetron minus intravenous ondansetron was larger than -15%. The non-inferiority margin was 15%.

Efficacy Results

As shown in Table 7, intravenous Palonosetron Hydrochloride Injection 20 mcg/kg (maximum 1.5 mg) demonstrated non-inferiority to the active comparator during the 0 to 24 hour time interval.

Table 7: Prevention of Acute Nausea and Vomiting (0-24 hours): Complete Response Rates
I.V. Palonosetron Hydrochloride Injection 20 mcg/kg (N=165) | I.V. Ondansetron 0.15 mg/kg x 3 (N=162) | Difference [97.5% Confidence Interval]*: I.V. Palonosetron Hydrochloride Injection minus I.V. Ondansetron Comparator
59.4% | 58.6% | 0.36% [-11.7%, 12.4%]
* To adjust for multiplicity of treatment groups, a lower-bound of a 97.5%
confidence interval was used to compare to -15%, the negative value of the non-inferiority margin.

In patients that received Palonosetron Hydrochloride Injection at a lower dose than the recommended dose of 20 mcg/kg, non-inferiority criteria were not met.

14.3 Postoperative Nausea and Vomiting

In one multicenter, randomized, stratified, double-blind, parallel-group, phase 3 clinical study (Study 1), palonosetron was compared with placebo for the prevention of PONV in 546 patients undergoing abdominal and gynecological surgery. All patients received general anesthesia. Study 1 was a pivotal study conducted predominantly in the US in the out-patient setting for patients undergoing elective gynecologic or abdominal laparoscopic surgery and stratified at randomization for the following risk factors: gender, non-smoking status, history of post operative nausea and vomiting and/or motion sickness.

In Study 1 patients were randomized to receive palonosetron 0.025 mg, 0.050 mg or 0.075 mg or placebo, each given intravenously immediately prior to induction of anesthesia. The antiemetic activity of palonosetron was evaluated during the 0 to 72 hour time period after surgery.

Of the 138 patients treated with 0.075 mg palonosetron in Study 1 and evaluated for efficacy, 96% were women; 66% had a history of PONV or motion sickness; 85% were non-smokers. As for race, 63% were White, 20% were Black, 15% were Hispanic, and 1% were Asian. The age of patients ranged from 21 to 74 years, with a mean age of 37.9 years. Three patients were greater than 65 years of age.

Co-primary efficacy measures were Complete Response (CR) defined as no emetic episode and no use of rescue medication in the 0-24 and in the 24-72 hours postoperatively.

Secondary efficacy endpoints included:

- Complete Response (CR) 0-48 and 0-72 hours
- Complete Control (CC) defined as CR and no more than mild nausea
- Severity of nausea (none, mild, moderate, severe)

The primary hypothesis in Study 1 was that at least one of the three palonosetron doses were superior to placebo.

Results for Complete Response in Study 1 for 0.075 mg palonosetron versus placebo are described in the following table.

Table 8: Prevention of Postoperative Nausea and Vomiting: Complete Response (CR), Study 1, Palonosetron 0.075 mg Vs Placebo
Treatment | n/N (%) | Palonosetron Vs Placebo
Treatment | n/N (%) | Δ | p-value*
Co-primary Endpoints
CR 0-24 hours
Palonosetron | 59/138 (42.8%) | 16.8% | 0.004
Placebo | 35/135 (25.9%)
CR 24-72 hours
Palonosetron | 67/138 (48.6%) | 7.8% | 0.188
Placebo | 55/135 (40.7%)
* To reach statistical significance for each co-primary endpoint, the required significance limit for the lowest p-value was p<0.017. Δ Difference (%): palonosetron 0.075 mg minus placebo

Palonosetron 0.075 mg reduced the severity of nausea compared to placebo. Analyses of other secondary endpoints indicate that palonosetron 0.075 mg was numerically better than placebo, however, statistical significance was not formally demonstrated.

A phase 2 randomized, double-blind, multicenter, placebo-controlled, dose ranging study was performed to evaluate I.V. palonosetron for the prevention of post-operative nausea and vomiting following abdominal or vaginal hysterectomy. Five I.V. palonosetron doses (0.1, 0.3, 1.0, 3.0 and 30 µg/kg) were evaluated in a total of 381 intent-to-treat patients. The primary efficacy measure was the proportion of patients with CR in the first 24 hours after recovery from surgery. The lowest effective dose was palonosetron 1 µg/kg (approximately 0.075 mg) which had a CR rate of 44% versus 19% for placebo, p=0.004. Palonosetron 1 µg/kg also significantly reduced the severity of nausea versus placebo, p=0.009.

16 HOW SUPPLIED/STORAGE AND HANDLING

NDC 69097-927-35, Palonosetron Hydrochloride Injection 0.25 mg/5 mL (free base) single-use vial individually packaged in a carton.

Storage

- Store at controlled temperature of 20–25°C (68°F–77°F). Excursions permitted to 15–30°C (59-86°F).
- Protect from freezing.
- Protect from light.

17 PATIENT COUNSELING INFORMATION

See FDA-approved patient labelling (Patient Information).

Instructions for Patients

Patients should be advised to report to their physician all of their medical conditions, including any pain, redness, or swelling in and around the infusion site [see Adverse Reactions (6.3)].

Advise patients of the possibility of serotonin syndrome, especially with concomitant use of Palonosetron Hydrochloride Injection and another serotonergic agent such as medications to treat depression and migraines. Advise patients to seek immediate medical attention if the following symptoms occur: changes in mental status, autonomic instability, neuromuscular symptoms with or without gastrointestinal symptoms [see Warnings and Precautions (5.2)].

Patients should be instructed to read the Patient Information.

Patient Information
PALONOSETRON HYDROCHLORIDE INJECTION
for Intravenous Use

Read this Patient Information before you receive Palonosetron Hydrochloride Injection and each time you receive Palonosetron Hydrochloride Injection. There may be new information. This information does not take the place of talking with your doctor about your medical condition or your treatment.

What is Palonosetron Hydrochloride Injection ?
Palonosetron Hydrochloride Injection is a prescription medicine called an "antiemetic."
Palonosetron Hydrochloride Injection is used in adults to help prevent the nausea and vomiting that happens:
• right away or later with certain anti-cancer medicines (chemotherapy)
• up to 24 hours while recovering from anesthesia after surgery
Palonosetron Hydrochloride Injection is used in children 1 month old to less than 17 years of age to help prevent the nausea and vomiting that happens right away with certain anti-cancer medicines (chemotherapy).
•It is not known if Palonosetron Hydrochloride Injection is safe and effective in children less than 1 month old to help prevent nausea and vomiting after chemotherapy.
•It is not known if Palonosetron Hydrochloride Injection is safe and effective in children for the prevention of nausea and vomiting while recovering from anesthesia after surgery.

Who should not receive Palonosetron Hydrochloride Injection ?
Do not receive Palonosetron Hydrochloride Injection if you are allergic to palonosetron hydrochloride or any of the ingredients in Palonosetron Hydrochloride Injection . See the end of this leaflet for a complete list of ingredients in Palonosetron Hydrochloride Injection .

What should I tell my doctor before receiving Palonosetron Hydrochloride Injection ?
Before receiving Palonosetron Hydrochloride Injection , tell your doctor about all of your medical conditions, including if you:
•have had an allergic reaction to another medicine for nausea or vomiting
•are pregnant or plan to become pregnant. It is not known if Palonosetron Hydrochloride Injection will harm your unborn baby.
•are breastfeeding or plan to breastfeed. It is not known if Palonosetron Hydrochloride Injection passes into your breast milk. You and your doctor should decide if you will receive Palonosetron Hydrochloride Injection if you breastfeed.
Tell your doctor about all of the medicines you take, including prescription and over-the-counter medicines, vitamins and herbal supplements.

How will I receive Palonosetron Hydrochloride Injection ?
•Palonosetron Hydrochloride Injection will be given to you in your vein by intravenous (I.V.) injection.
•Palonosetron Hydrochloride Injection is usually given about 30 minutes before you receive your anti-cancer medicine (chemotherapy) or right before anesthesia for surgery.

What are the possible side effects of Palonosetron Hydrochloride Injection ?
Palonosetron Hydrochloride Injection can cause allergic reactions that can sometimes be serious. Tell your doctor or nurse right away if you have any of the following symptoms of a serious allergic reaction with Palonosetron Hydrochloride Injection:
•hives
•swollen face
•breathing trouble
•chest pain
The most common side effects of Palonosetron Hydrochloride Injection in adults are headache and constipation.
These are not all the possible side effects from Palonosetron Hydrochloride Injection. Call your doctor for medical advice about side effects. You may report side effects to FDA at 1-800-FDA-1088

General information about the safe and effective use of Palonosetron Hydrochloride Injection
Medicines are sometimes prescribed for purposes other than those listed in a Patient Information leaflet. You can ask your doctor or pharmacist for information about Palonosetron Hydrochloride Injection that is written for health professionals.

What are the ingredients in Palonosetron Hydrochloride Injection?
Active ingredient: palonosteron hydrochloride
Inactive ingredients: mannitol, disodium edetate, and citrate buffer in water
Mfd by: OSO Biopharmaceuticals, LLC, Albuquerque, NM, USA or Pierre Fabre, Médicament Production, Idron, Aquitaine, France and Helsinn Birex Pharmaceuticals Ltd, Dublin, Ireland.
Distributed and Marketed by:
Cipla USA, Inc.
1560 Sawgrass Corporate Parkway,
Suite 130, Sunrise, FL 33323
For more information, call 1-866-604-3268
Under license of Helsinn Healthcare SA, Switzerland
This Patient Information has been approved by the U.S. Food and Drug Administration.
Revised: 1/2018

PACKAGE LABEL.PRINCIPAL DISPLAY PANEL

GTIN 00369097927356

NDC 69097-927-35

Palonosetron HCl Injection

0.25 mg/5 mL (0.05 mg/mL)

For intravenous injection only.

5 mL single-use sterile vial.

Discard unused portion.

Cipla

Distributed and Marketed by:

Cipla USA, Inc. 1560 Sawgrass Corporate Parkway, Suite 130, Sunrise, FL 33323

under license of Helsinn Healthcare SA, Switzerland.

Store at controlled temperature of 20–25°C (68°F–77°F).

Excursions permitted to 15–30°C (59-86°F). (see USP)

Protect from light.

See package insert for dosage and administration information.

Rx Only

Contents: Each mL of aqueous solution contains palonosetron hydrochloride equivalent to 0.05 mg of palonosetron. Each mL also contains 41.5 mg mannitol, 0.05 mg edetate disodium dihydrate, 3.7 mg trisodium citrate dihydrate, 1.56 mg citric acid monohydrate and water for injection (q.s to 1.0 mL). Hydrochloric acid or sodium hydroxide may have been added to adjust pH.

Jointly manufactured by OSO Biopharmaceuticals, LLC, Albuquerque, NM, USA or Pierre Fabre, Medicament Production, Idron, Aquitaine, France and Helsinn Birex Pharmaceuticals Ltd, Dublin, Ireland.

carton-label

NDC 69097-927-35 Rx only

Palonosetron HCl Injection

0.25 mg/5 mL (0.05 mg/mL)

For intravenous injection only.

5 mL single-use sterile vial.

Store at 20–25°C (68°F–77°F).

Protect from light.

Cipla

Distributed and Marketed by:

Cipla USA, Inc. 1560 Sawgrass Corporate Parkway, Suite 130, Sunrise, FL 33323

container-label